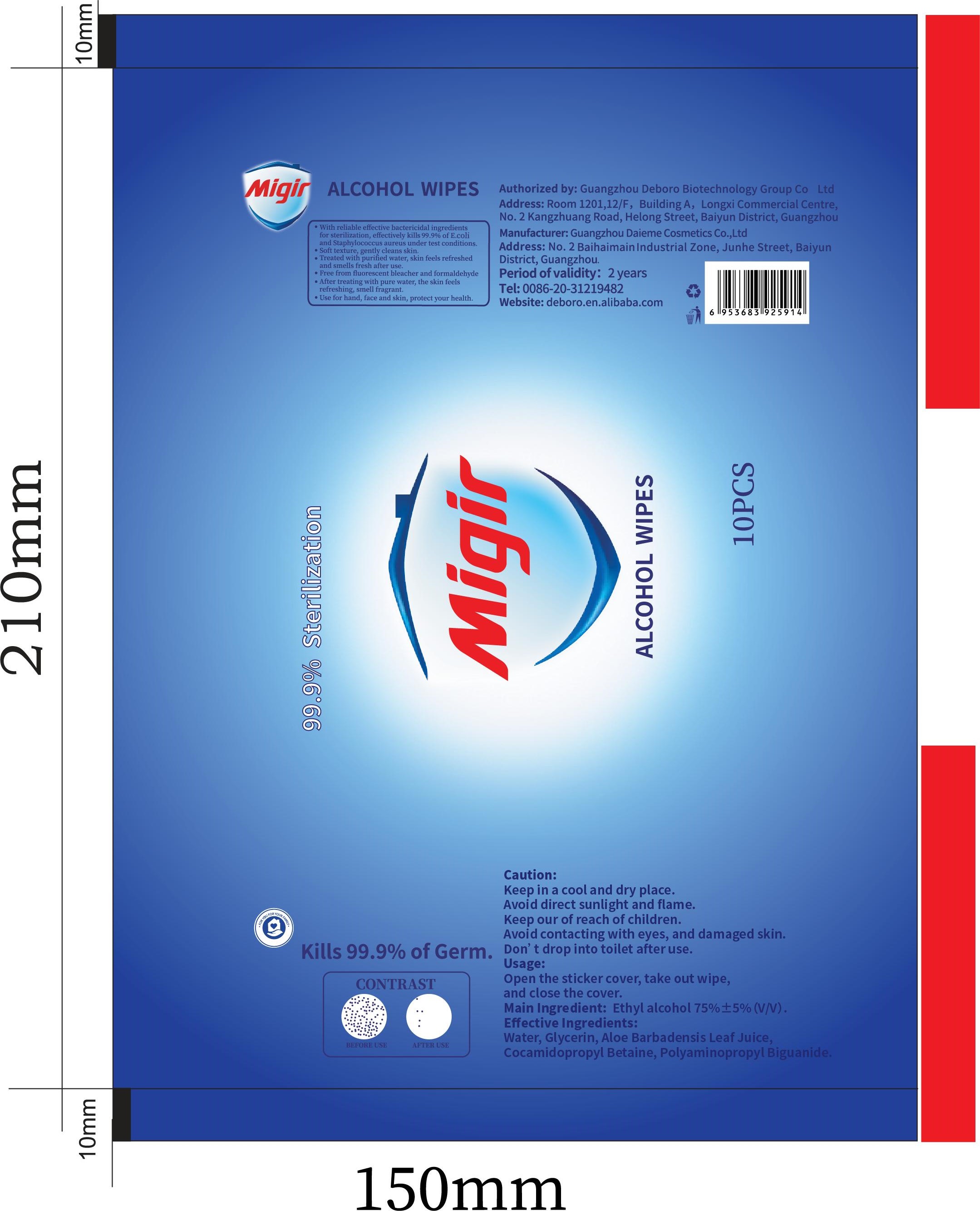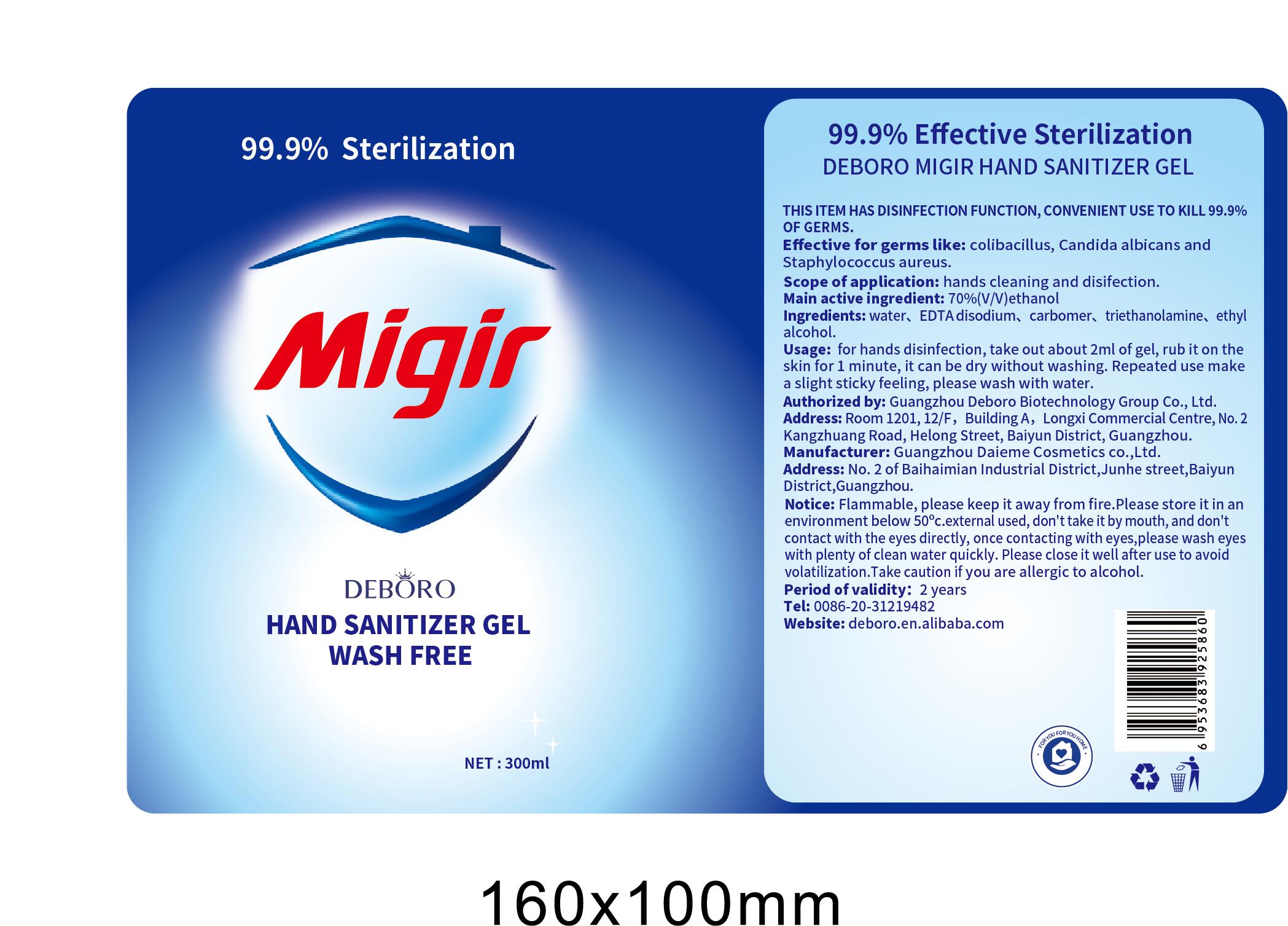 DRUG LABEL: Wipes
NDC: 54237-033 | Form: CLOTH
Manufacturer: Guangzhou Daieme Cosmetic Co,.Ltd
Category: otc | Type: HUMAN OTC DRUG LABEL
Date: 20210223

ACTIVE INGREDIENTS: ALCOHOL 34.9 g/100 g
INACTIVE INGREDIENTS: GLYCERIN; POLYAMINOPROPYL BIGUANIDE; WATER

Main active ingredient

70%(v/v) ethanol

- THIS ITEM HAS DISINFECTION FUNCTION, CONVENIENT USE TO KILL 99.9% OF GERMS.
- Effective for germs like: colibasillus. Candida albicans anc Staphylococcus aureus.
- Scope of application: hands cleaning and disifection.
- Main active ingredient: 70%(V/V)ethanol
- Ingredients: water, EDTA disodium, carbomer, triethanolamine, ethyalcohol.
- Usage: for hands disinfection, take out about 2ml of gel, rub it on the skin for 1 minute, it can be dry without washing. Repeated use make a slight sticky feeling, please wash with water.
- Notice: Flammable, please keep it away from fire.Please store it in an environment below 50℃.external used, don't take it by mouth, and don't contact with the eyes directly, once contacting with eyes,please wash eyes with plenty of clean water quickly. Please close it well after use to avoid volatilization.Take caution if you are allergic to alcohol.
- Period of validity: 2 years

Scope of application

Hands cleaning and disifection

Usage

for hands disinfection, take out about 2ml of gel, rub it on the skin for 1 minute, it can be dry without washing. Repeated use make a slight sticky feeling, please wash with water.

Notice

Flammable, please keep it away from fire.Please store it in an environment below 50℃.external used, don'ttake it by mouth, and don't contact with the eyes directly, once contacting with eyes,please wash eyes with plenty of clean water quickly. Please close it well after use to avoid volatilization.Take caution if you are allergic to alcohol.

Do not use

- Avoid contacting with eyes, and damaged skin

WHEN USING

Flammable, please keep it away from fire.Please store it in an environment below 50°c.external used, don'ttake it by mouth, and don't contact with the eyes directly, once contacting with eyes,please wash eyes with plenty of clean water quickly. Please close it well after use to avoid volatilization.Take caution if you are allergic to alcohol.

STOP USE

Take caution if you are allergic to alcohol.

KEEP OUT OF REACH OF CHILDREN

Keep our of reach of children. Avoid contacting with eyes, and damaged skin

Directions

Avoid contacting with eyes, and damaged skin

Other information

Please store it in an environment below 50 ℃

ingredients

water, EDTA disodium, carbomer, triethanolamine, ethyl alcohol.

Package label

Hand sanitizer gel:

2ml NDC: 54237-032-01

30ml NDC: 54237-032-02

60ml NDC: 54237-032-03

99ml NDC: 54237-032-04

100ml NDC: 54237-032-05

120ml NDC: 54237-032-06

300ml NDC: 54237-032-07

500ml NDC: 54237-032-08

1L NDC: 54237-032-09

1oz NDC: 54237-032-10

4oz NDC: 54237-032-11

8oz NDC: 54237-032-12

16oz NDC: 54237-032-13

Wipes:

1pcs NDC: 54237-033-01

8pcs NDC: 54237-033-02

10pcs NDC: 54237-033-03

20pcs NDC: 54237-033-04

25pcs NDC: 54237-033-05

48pcs NDC: 54237-033-06

50pcs NDC: 54237-033-07

80pcs NDC: 54237-033-08

100pcs NDC: 54237-033-09